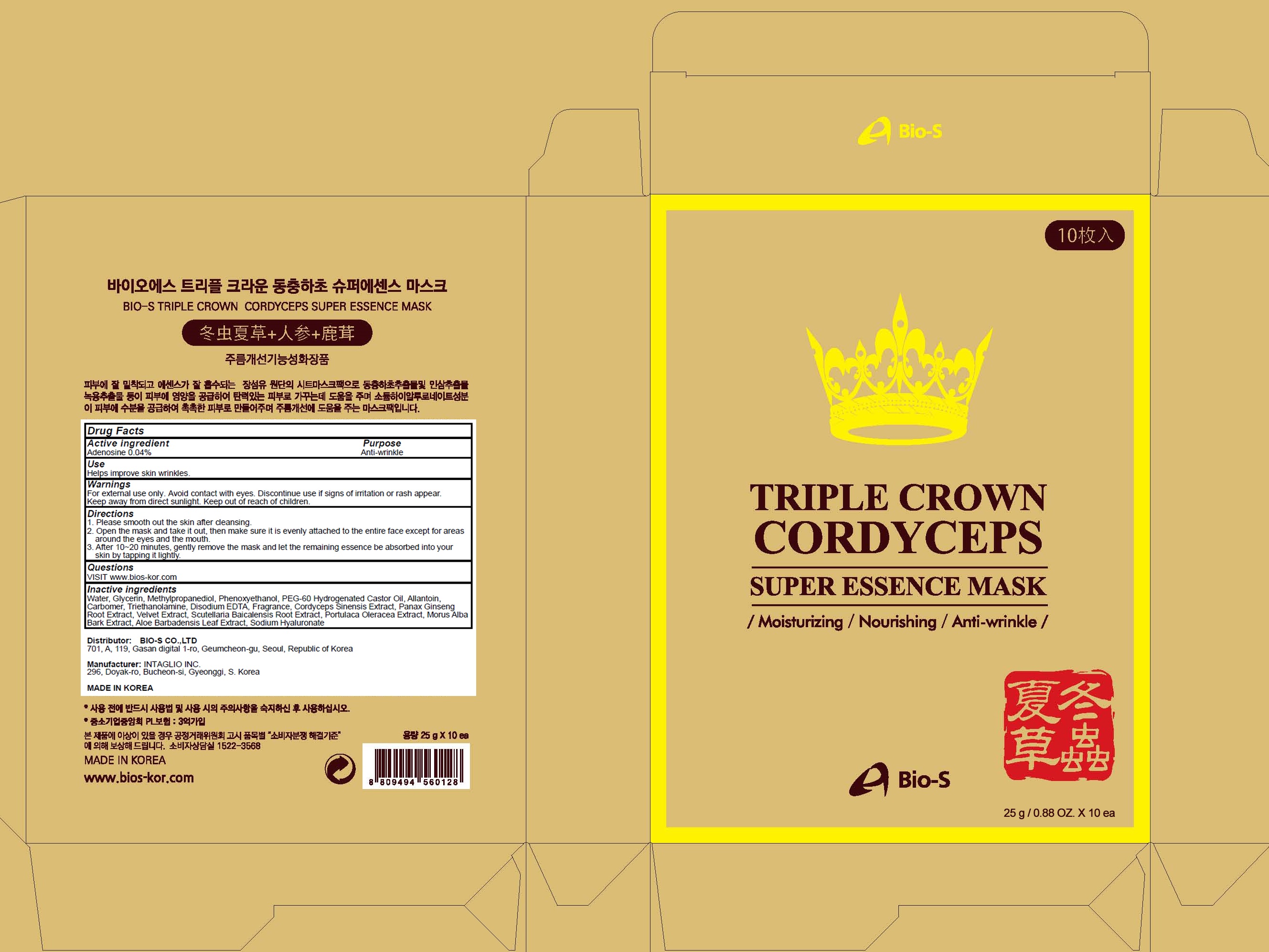 DRUG LABEL: TRIPLE CROWN CORDYCEPS SUPER ESSENCE MASK
NDC: 81211-050 | Form: PATCH
Manufacturer: BIO-S CO.,LTD
Category: otc | Type: HUMAN OTC DRUG LABEL
Date: 20201215

ACTIVE INGREDIENTS: Adenosine 0.01 g/25 g
INACTIVE INGREDIENTS: Water; Glycerin; Methylpropanediol; Phenoxyethanol; PEG-60 HYDROGENATED CASTOR OIL; Allantoin

ACTIVE INGREDIENT

Adenosine 0.04%

PURPOSE

Anti-wrinkle

Use

Helps improve skin wrinkles.

WARNINGS

For external use only.
Avoid contact with eyes.
Discontinue use if signs of irritation or rash appear.
Keep away from direct sunlight.
Replace the cap after use.
Keep out of reach of children.

KEEP OUT OF REACH OF CHILDREN

Direction

1. Please smooth out the skin after cleansing.
2. Open the mask and take it out, then make sure it is evenly attached to the entire face except for areas around the eyes and the mouth.
3. After 10~20 minutes, gently remove the mask and let the remaining essence be absorbed into your skin by tapping it lightly.

QUESTIONS

VISIT www.bios-kor.com

INACTIVE INGREDIENTS

Water, Glycerin, Methylpropanediol, Phenoxyethanol, PEG-60 Hydrogenated Castor Oil, Allantoin, Carbomer, Triethanolamine, Disodium EDTA, Fragrance, Cordyceps Sinensis Extract, Panax Ginseng Root Extract, Velvet Extract, Scutellaria Baicalensis Root Extract, Portulaca Oleracea Extract, Morus Alba Bark Extract, Aloe Barbadensis Leaf Extract, Sodium Hyaluronate